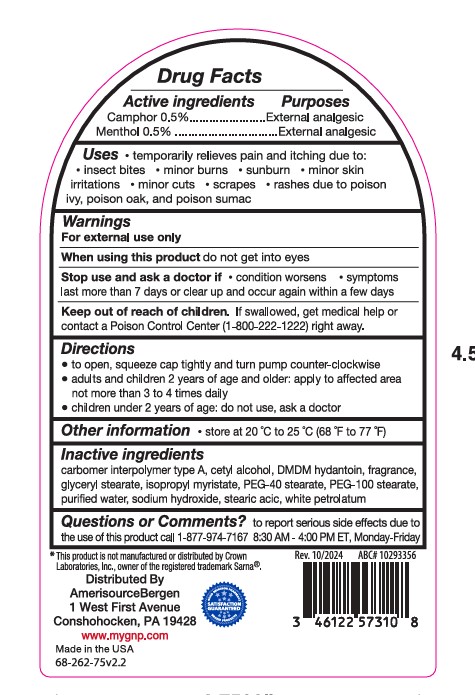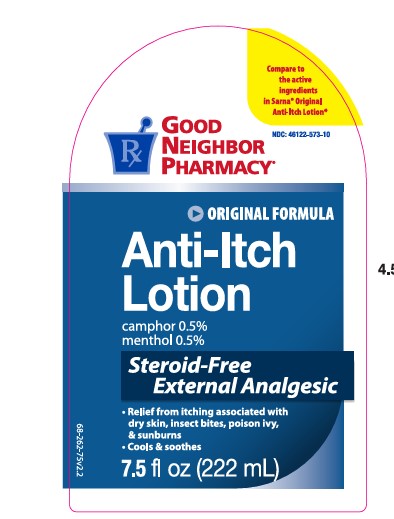 DRUG LABEL: GNP Anti Itch
NDC: 46122-573 | Form: LOTION
Manufacturer: AMERISOURCEBERGEN DRUG CORPORATION
Category: otc | Type: HUMAN OTC DRUG LABEL
Date: 20241223

ACTIVE INGREDIENTS: MENTHOL 0.5 g/100 g; CAMPHOR (SYNTHETIC) 0.5 g/100 g
INACTIVE INGREDIENTS: PEG-40 STEARATE; STEARIC ACID; CARBOMER 940; SODIUM HYDROXIDE; DMDM HYDANTOIN; ISOPROPYL MYRISTATE; CETYL ALCOHOL; PEG-100 STEARATE; GLYCERYL STEARATE SE; PETROLATUM; WATER

GNP Original Anti-Itch Lotion

Active Ingredients

Camphor 0.5%............................................................................................................................ External analgesic

Menthol 0.5%.............................................................................................................................. External analgesic

Uses

temporary relieves pain and itching due to:

insect bites

minor burns

sunburn

minor skin irritations

minor cuts

scrapes

rashes due to poison ivy, poison oak, and poison sumac

Warning

For external use only

Ask doctor before use

on chicken pox

on measles

when using this product

do not get into eyes

Stop Use and ask doctor if

condition worsens

symptoms last more than 7 days or clear up and occur again within a few days

Keep out of reach of children

If swallowed, get medical help or contact a Poison Control Center right away.

Purpose

Anti - itch

Directions

to open, squeeze cap tightly and turn pump counter-clockwise

adults and children 2 years and older: apply to affected area not more than 3 to 4 times daily

children under 2 years: ask a doctor

Other information

store at 20 °C to 25 °C (68 °F to 77 °F)

Inactive ingredients

carbomer 940, cetyl alcohol, DMDM hydantoin, fragrance, glyceryl stearate, isopropyl myristate, PEG-40 stearate, PEG-100 stearate,
purified water, sodium hydroxide, stearic acid, white petrolatum.